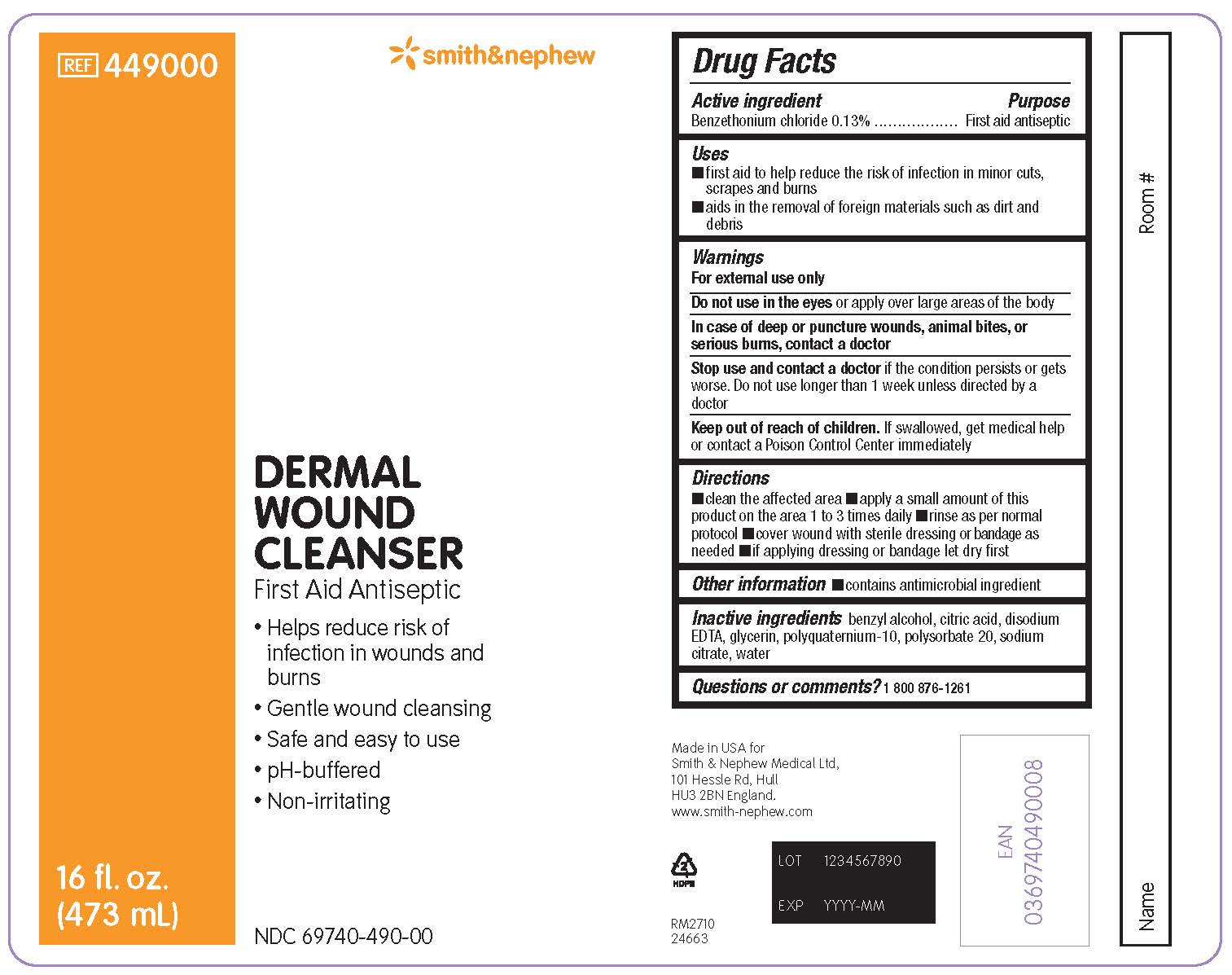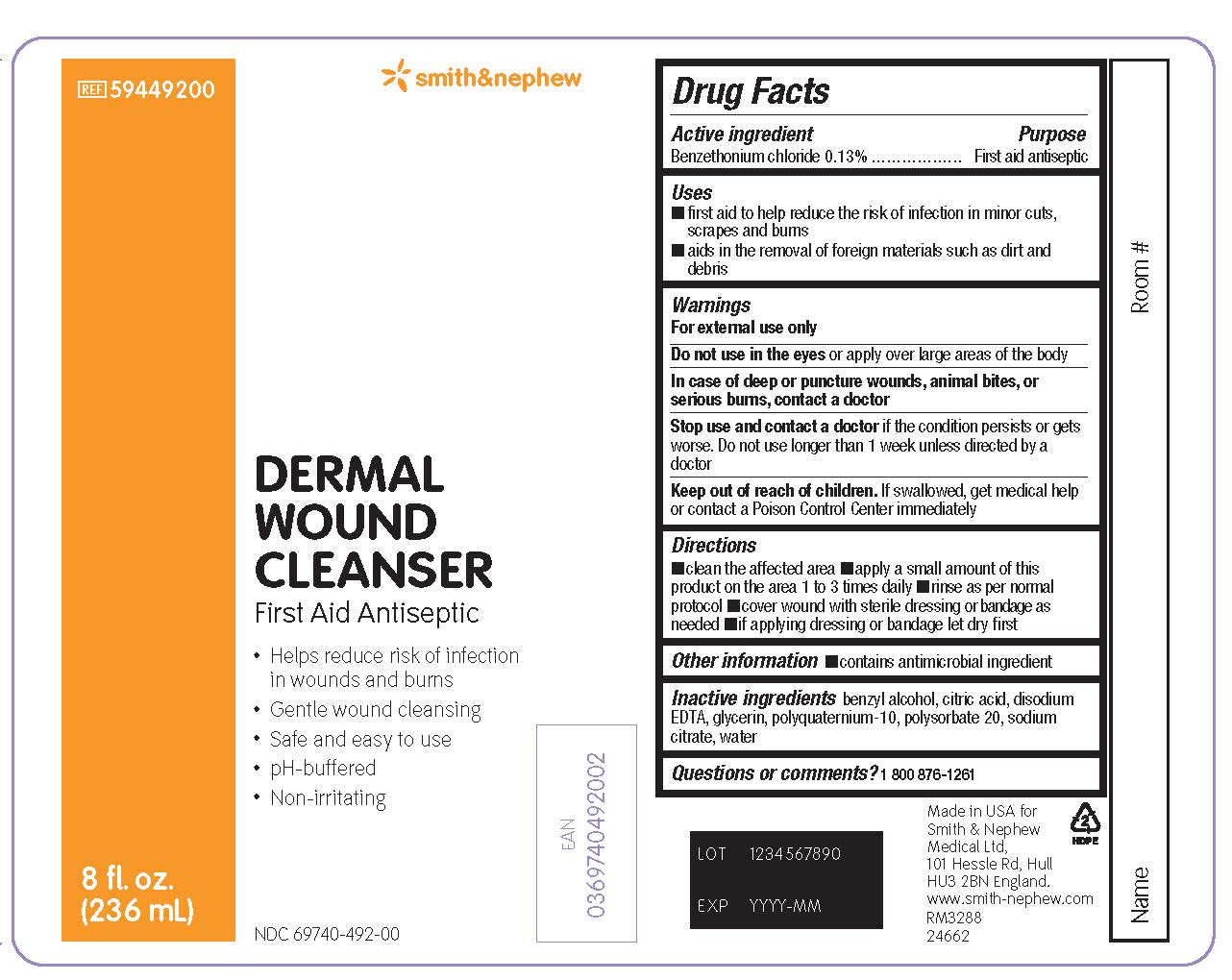 DRUG LABEL: Dermal Wound Cleanser
NDC: 69740-490 | Form: SPRAY
Manufacturer: Smith & Nephew Medical Ltd.
Category: otc | Type: HUMAN OTC DRUG LABEL
Date: 20240715

ACTIVE INGREDIENTS: BENZETHONIUM CHLORIDE 1.3 g/981 mL
INACTIVE INGREDIENTS: BENZYL ALCOHOL; EDETATE DISODIUM; GLYCERIN; POLYSORBATE 20; WATER; SODIUM CITRATE; ANHYDROUS CITRIC ACID; POLYQUATERNIUM-10 (125 MPA.S AT 2%)

Dermal Wound Cleanser

ACTIVE INGREDIENTS

Benzethonium Chloride 0.13%

PURPOSE

First aid antiseptic

USES

- first aid to help reduce the risk of infection in minor cuts, scrapes and burns
- aids in the removal of foreign materials such as dirt and debris

WARNINGS

- For external use only
- Do not use in the eyes or apply over large areas of the body
- In case of deep or puncture wounds, animal bites, or serious burns, contact a doctor
- Stop use and contact a doctor if the condition persists or gets worse. Do not use longer than 1 week unless directed by a doctor
- Keep out of reach of children. If swallowed, get medical help or contact a Poison Control Center immediately

WHEN USING

- For external use only

- Do not use in the eyesor apply over large areas of the body

STOP USE

- In case of deep or puncture wounds, animal bites, or serious burns, contact a doctor
- Stop use and contact a doctorif the condition persists or gets worse. Do not use longer than 1 week unless directed by a doctor

- Keep out of reach of children. If swallowed, get medical help or contact a Poison Control Center immediately

DIRECTIONS

- clean the affected area
- apply a small amount of this product on the area 1 to 3 times daily
- rinse as per normal protocol
- cover wound with sterile dressing or bandage as needed
- if applying dressing or bandage, let dry first

OTHER INFORMATION

- contains antimicrobial ingredient

INACTIVE INGREDIENTS

benzyl alcohol, citric acid, disodium EDTA, glycerin, polyquaternium-10, polysorbate 20, sodium citrate, water

QUESTION OR COMMENTS?

1 800 876-1261

PACKAGE LABEL - PRINCIPAL DISPLAY PANEL - DERMAL WOUND CLEANSER BOTTLE, SPRAY (473 mL)

Smith&Nephew

REF 449000
NDC69740-490-00

Dermal
Wound
Cleanser

First Aid Antiseptic

- Helps reduce risk of infection in wounds and burns
- Gentle wound cleansing
- Safe and easy to use
- pH-buffered
- Non-irritating

16 fl. oz. (473 mL)

Made in the USA for Smith & Nephew Medical Ltd.
101 Hessle Road
Hull
HU3 2BN
England
www.smith-nephew.com

PACKAGE LABEL - PRINCIPAL DISPLAY PANEL - DERMAL WOUND CLEANSER BOTTLE, SPRAY (236 mL)

Smith&Nephew

#59449200

NDC 69740-492-00

Dermal
Wound
Cleanser

First Aid Antiseptic

- Helps reduce risk of infection in wounds and burns
- Gentle wound cleansing
- Safe and easy to use
- pH-buffered
- Non-irritating

8 fl. oz. (236 mL)

Made in the USA for Smith & Nephew Medical Ltd.
101 Hessle Road
Hull
HU3 2BN
England
www.smith-nephew.com